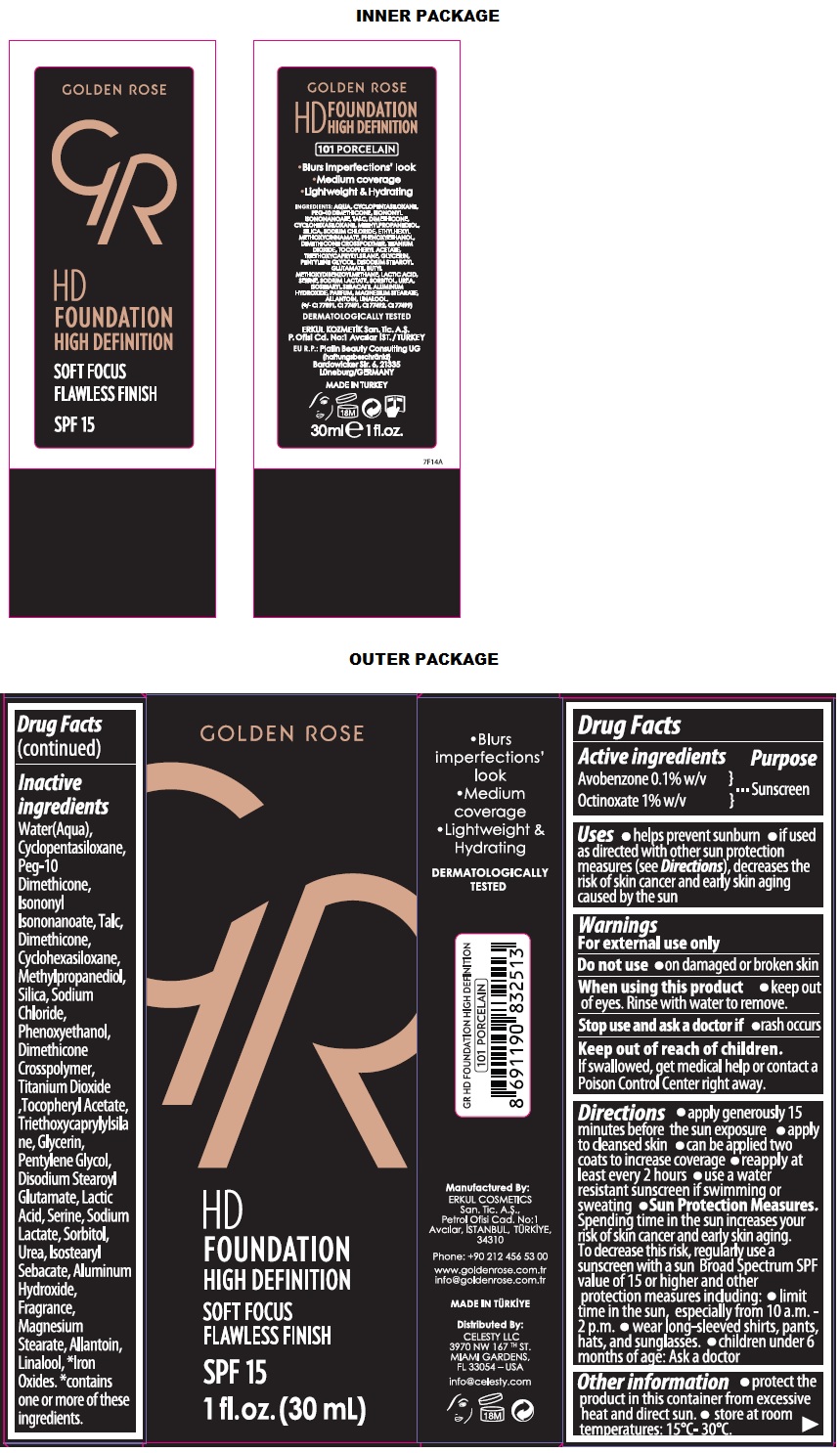 DRUG LABEL: GR HD FOUNDATION HIGH DEFINITION SPF 15
NDC: 82715-105 | Form: LOTION
Manufacturer: ERKUL KOZMETIK SANAYI VE TICARET ANONIM SIRKETI
Category: otc | Type: HUMAN OTC DRUG LABEL
Date: 20250806

ACTIVE INGREDIENTS: AVOBENZONE 0.1 g/100 mL; OCTINOXATE 1 g/100 mL
INACTIVE INGREDIENTS: WATER; CYCLOMETHICONE 5; PEG-10 DIMETHICONE (600 CST); ISONONYL ISONONANOATE; TALC; DIMETHICONE, UNSPECIFIED; CYCLOMETHICONE 6; METHYLPROPANEDIOL; SILICON DIOXIDE; SODIUM CHLORIDE; PHENOXYETHANOL; DIMETHICONE CROSSPOLYMER (450000 MPA.S); TITANIUM DIOXIDE; .ALPHA.-TOCOPHEROL ACETATE; TRIETHOXYCAPRYLYLSILANE; GLYCERIN; PENTYLENE GLYCOL; DISODIUM STEAROYL GLUTAMATE; LACTIC ACID, UNSPECIFIED FORM; SERINE; SODIUM LACTATE; SORBITOL; UREA; ISOSTEARYL SEBACATE; ALUMINUM HYDROXIDE; MAGNESIUM STEARATE; ALLANTOIN; LINALOOL, (+/-)-; FERRIC OXIDE RED; FERRIC OXIDE YELLOW; FERROSOFERRIC OXIDE

GR GOLDEN ROSE HD FOUNDATION HIGH DEFINITION

Active ingredients

Avobenzone 0.1% w/v
Octinoxate 1% w/v

Purpose

Sunscreen

Uses

• helps prevent sunburn • if used as directed with other sun protection measures (see Directions), decreases the risk of skin cancer and early skin aging caused by the sun

Warnings

For external use only

Do not use • on damaged or broken skin

When using this product • keep out of eyes. Rinse with water to remove.

Stop use and ask a doctor if • rash occurs

Keep out of reach of children. If swallowed, get medical help or contact a Poison Control Center right away.

Directions

• apply generously 15 minutes before the sun exposure • apply to cleansed skin • can be applied two coats to increase coverage • reapply at least every 2 hours • use a water resistant sunscreen if swimming or sweating • Sun Protection Measures. Spending time in the sun increases your risk of skin cancer and early skin aging. To decrease this risk, regularly use a sunscreen with a sun Broad Spectrum SPF value of 15 or higher and other protection measures including: • limit time in the sun, especially from 10 a.m. - 2 p.m. • wear long-sleeved shirts, pants, hats, and sunglasses. • children under 6 months of age: Ask a doctor

Other information

• protect the product in this container from excessive heat and direct sun. • store at room temperatures: 15°C- 30°C.

Inactive ingredients

Water(Aqua), Cyclopentasiloxane, Peg-10 Dimethicone, Isononyl Isononanoate, Talc, Dimethicone, Cyclohexasiloxane, Methylpropanediol, Silica, Sodium Chloride, Phenoxyethanol, Dimethicone Crosspolymer, Titanium Dioxide, Tocopheryl Acetate, Triethoxycaprylylsilane, Glycerin, Pentylene Glycol, Disodium Stearoyl Glutamate, Lactic Acid, Serine, Sodium Lactate, Sorbitol, Urea, Isostearyl Sebacate, Aluminum Hydroxide, Fragrance, Magnesium Stearate, Allantoin, Linalool, *Iron Oxides. *contains one or more of these ingredients.

GOLDEN ROSE

SOFT FOCUS FLAWLESS FINISH

SPF 15

• Blurs imperfections' look
• Medium coverage
• Lightweight & Hydrating

DERMATOLOGICALLY TESTED

101 PORCELAIN

Manufactured By:
ERKUL COSMETICS San. Tic. A.Ş.,
Petrol Ofisi Cad. No:1
Avcılar, ISTANBUL, TURKIYE,
34310

Phone: +90 212 456 53 00

www.goldenrose.com.tr
info@goldenrose.com.tr

MADE IN TURKIYE

Distributed By:
CELESTY LLC
3970 NW 167TH ST.
MIAMI GARDENS,
FL 33054 – USA

info@celesty.com

EU R.P: Platin Beauty Consulting UG (haftungsbeschränkt)
Bardowicker Str. 6, 21335
Lüneburg/GERMANY